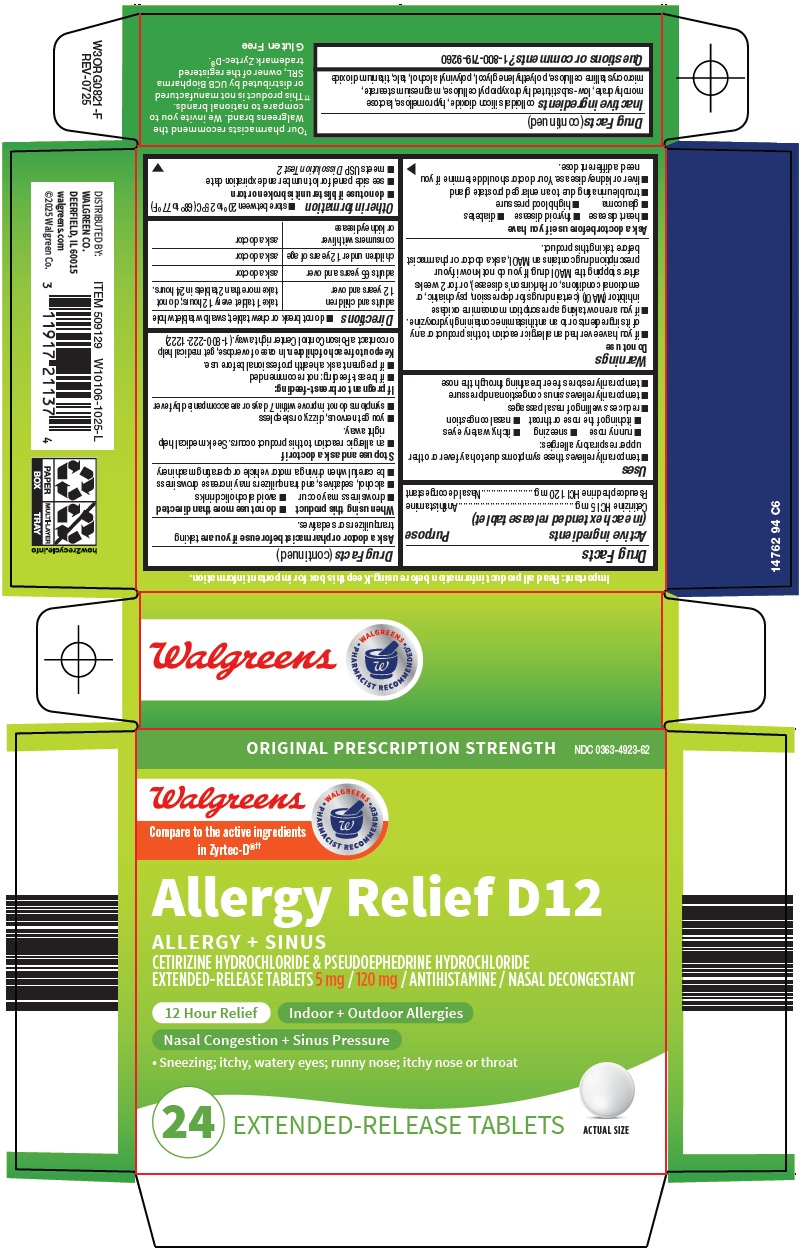 DRUG LABEL: allergy relief D12
NDC: 0363-4923 | Form: TABLET, FILM COATED, EXTENDED RELEASE
Manufacturer: Walgreen Company
Category: otc | Type: HUMAN OTC DRUG LABEL
Date: 20260228

ACTIVE INGREDIENTS: CETIRIZINE HYDROCHLORIDE 5 mg/1 1; PSEUDOEPHEDRINE HYDROCHLORIDE 120 mg/1 1
INACTIVE INGREDIENTS: SILICON DIOXIDE; HYPROMELLOSE, UNSPECIFIED; LACTOSE MONOHYDRATE; LOW-SUBSTITUTED HYDROXYPROPYL CELLULOSE, UNSPECIFIED; MAGNESIUM STEARATE; MICROCRYSTALLINE CELLULOSE; POLYETHYLENE GLYCOL, UNSPECIFIED; POLYVINYL ALCOHOL, UNSPECIFIED; TALC; TITANIUM DIOXIDE

Walgreen Co. Allergy Relief D12 Drug Facts

Active ingredients (in each extended release tablet)

Cetirizine HCl 5 mg

Pseudoephedrine HCl 120 mg

Purpose

Antihistamine

Nasal decongestant

Uses

- temporarily relieves these symptoms due to hay fever or other upper respiratory allergies:
  - runny nose
  - sneezing
  - itchy, watery eyes
  - itching of the nose or throat
  - nasal congestion
- reduces swelling of nasal passages
- temporarily relieves sinus congestion and pressure
- temporarily restores freer breathing through the nose

Warnings

Do not use

- if you have ever had an allergic reaction to this product or any of its ingredients or to an antihistamine containing hydroxyzine.
- if you are now taking a prescription monoamine oxidase inhibitor (MAOI) (certain drugs for depression, psychiatric, or emotional conditions, or Parkinson’s disease), or for 2 weeks after stopping the MAOI drug. If you do not know if your prescription drug contains an MAOI, ask a doctor or pharmacist before taking this product.

Ask a doctor before use if you have

- heart disease
- thyroid disease
- diabetes
- glaucoma
- high blood pressure
- trouble urinating due to an enlarged prostate gland
- liver or kidney disease. Your doctor should determine if you need a different dose.

Ask a doctor or pharmacist before use if you are

taking tranquilizers or sedatives.

When using this product

- do not use more than directed
- drowsiness may occur
- avoid alcoholic drinks
- alcohol, sedatives, and tranquilizers may increase drowsiness
- be careful when driving a motor vehicle or operating machinery

Stop use and ask a doctor if

- an allergic reaction to this product occurs. Seek medical help right away.
- you get nervous, dizzy, or sleepless
- symptoms do not improve within 7 days or are accompanied by fever

If pregnant or breast-feeding:

- if breast-feeding: not recommended
- if pregnant: ask a health professional before use.

Directions

- do not break or chew tablet; swallow tablet whole

adults and children 12 years and over | take 1 tablet every 12 hours; do not take more than 2 tablets in 24 hours.
adults 65 years and over | ask a doctor
children under 12 years of age | ask a doctor
consumers with liver or kidney disease | ask a doctor

Other information

- store between 20° to 25°C (68° to 77°F)
- do not use if blister unit is broken or torn
- see side panel for lot number and expiration date
- meets USP Dissolution Test 2

Inactive ingredients

colloidal silicon dioxide, hypromellose, lactose monohydrate, low-substituted hydroxypropyl cellulose, magnesium stearate, microcrystalline cellulose, polyethylene glycol, polyvinyl alcohol, talc, titanium dioxide

Questions or comments?

1-800-719-9260

Package/Label Principal Display Panel

ORIGINAL PRESCRIPTION STRENGTH

Walgreens

WALGREENS PHARMACIST RECOMMENDED

Compare to the active ingredients in Zyrtec-D®

Allergy Relief D12

ALLERGY + SINUS

CETIRIZINE HYDROCHLORIDE & PSEUDOEPHEDRINE HYDROCHLORIDE EXTENDED-RELEASE TABLETS 5 mg / 120 mg / ANTIHISTAMINE / NASAL DECONGESTANT

12 Hour Relief

Indoor + Outdoor Allergies

Nasal Congestion + Sinus Pressure

• Sneezing; itchy, watery eyes; runny nose; itchy nose or throat

24 EXTENDED-RELEASE TABLETS

ACTUAL SIZE